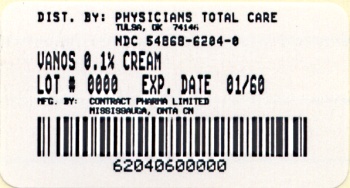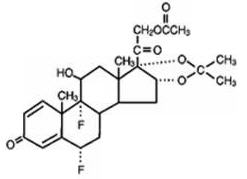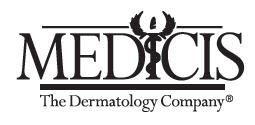 DRUG LABEL: Vanos
NDC: 54868-6204 | Form: CREAM
Manufacturer: Physicians Total Care, Inc.
Category: prescription | Type: HUMAN PRESCRIPTION DRUG LABEL
Date: 20100204

ACTIVE INGREDIENTS: FLUOCINONIDE 1 mg/1 g
INACTIVE INGREDIENTS: PROPYLENE GLYCOL; DIMETHYL ISOSORBIDE; POLYOXYL 100 STEARATE; GLYCERYL MONOSTEARATE; WATER; CARBOMER HOMOPOLYMER TYPE C; DIISOPROPANOLAMINE; CITRIC ACID MONOHYDRATE

VANOS®
(fluocinonide) Cream, 0.1%

Rx Only

FOR TOPICAL USE ONLY
NOT FOR OPHTHALMIC, ORAL, OR INTRAVAGINAL USE

DESCRIPTION

VANOS (fluocinonide) Cream, 0.1% contains fluocinonide, a synthetic corticosteroid for topical dermatologic use. The corticosteroids constitute a class of primarily synthetic steroids used topically as anti-inflammatory and antipruritic agents. Fluocinonide has the chemical name 6 alpha, 9 alpha-difluoro-11 beta, 21-dihydroxy-16 alpha, 17 alpha-isopropylidenedioxypregna-1, 4-diene-3,20-dione 21-acetate. Its chemical formula is C26H32F2O7 and it has a molecular weight of 494.58.

It has the following chemical structure:

Fluocinonide is an almost odorless white to creamy white crystalline powder. It is practically insoluble in water and slightly soluble in ethanol.

Each gram of VANOS Cream contains 1 mg micronized fluocinonide in a cream base of propylene glycol USP, dimethyl isosorbide, glyceryl stearate (and) PEG-100 stearate, glyceryl monostearate NF, purified water USP, carbopol 980 NF, diisopropanolamine, and citric acid USP.

CLINICAL PHARMACOLOGY

Like other topical corticosteroids, VANOS (fluocinonide) Cream, has anti-inflammatory, antipruritic, and vasoconstrictive properties. The mechanism of the anti-inflammatory activity of topical corticosteroids, in general, is unclear. However, corticosteroids are thought to act by induction of phospholipase A2 inhibitory proteins, collectively called lipocortins. It is postulated that these proteins control the biosynthesis of potent mediators of inflammation such as prostaglandins and leukotrienes by inhibiting the release of their common precursor, arachadonic acid. Arachadonic acid is released from membrane phospholipids by phospholipase A2.

Pharmacokinetics

The extent of percutaneous absorption of topical corticosteroids is determined by many factors including the vehicle and the integrity of the epidermal barrier. Topical corticosteroids can be absorbed from normal intact skin. Inflammation and/or other disease processes in the skin may increase percutaneous absorption.

Vasoconstrictor studies performed with VANOS Cream, 0.1% in healthy subjects indicate that it is in the super-high range of potency as compared with other topical corticosteroids; however, similar blanching scores do not necessarily imply therapeutic equivalence.

Application of VANOS Cream, 0.1% twice daily for 14 days in 18 adult patients with plaque-type psoriasis (10–50% BSA, mean 19.6% BSA) showed demonstrable HPA-axis suppression in 2 patients (with 12% and 25% BSA) where the criterion for HPA-axis suppression is a serum cortisol level of less than or equal to 18 micrograms per deciliter 30 minutes after stimulation with cosyntropin (ACTH1–24) (See PRECAUTIONS: General and Pediatric Use).

HPA-axis suppression has not been evaluated in psoriasis patients who are less than 18 years of age. HPA-axis suppression has been evaluated in pediatric patients with atopic dermatitis 12 to 18 years of age (See PRECAUTIONS: Pediatric Use).

CLINICAL STUDIES

Two adequate and well-controlled efficacy and safety studies of VANOS Cream have been completed, one in adult patients with plaque-type psoriasis (Table 1), and one in adult patients with atopic dermatitis (Table 2). In each of these studies, patients with between 2% and 10% body surface area involvement at Baseline treated all affected areas either once daily or twice daily with VANOS Cream for 14 consecutive days. The primary measure of efficacy was the proportion of patients whose condition was cleared or almost cleared at the end of treatment. The results of these studies are presented in the tables below as percent and number of patients achieving treatment success at Week 2.

Table 1: Plaque-Type Psoriasis in Adults
 | VANOS Cream, once daily (n=107) | Vehicle, once daily (n=54) | VANOS Cream, twice daily (n=107) | Vehicle, twice daily (n=55)
Patients cleared | 0 (0) | 0 (0) | 6 (6%) | 0 (0)
Patients achieving treatment success [Cleared or almost cleared] | 19 (18%) | 4 (7%) | 33 (31%) | 3 (5%)

Table 2: Atopic Dermatitis in Adults
 | VANOS Cream, once daily (n=109) | Vehicle, once daily (n=50) | VANOS Cream, twice daily (n=102) | Vehicle, twice daily (n=52)
Patients cleared | 11 (10%) | 0 (0) | 17 (17%) | 0 (0)
Patients achieving treatment success [Cleared or almost cleared] | 64 (59%) | 6 (12%) | 58 (57%) | 10 (19%)

No efficacy studies have been conducted to compare VANOS (fluocinonide) Cream, 0.1% with any other topical corticosteroid product, including fluocinonide cream 0.05%.

INDICATIONS AND USAGE

VANOS (fluocinonide) Cream, 0.1%, is a corticosteroid indicated for the relief of the inflammatory and pruritic manifestations of corticosteroid responsive dermatoses in patients 12 years of age or older (See PRECAUTIONS: Pediatric Use).

Treatment beyond 2 consecutive weeks is not recommended and the total dosage should not exceed 60 g/week because the safety of VANOS Cream for longer than 2 weeks has not been established and because of the potential for the drug to suppress the hypothalamic-pituitary-adrenal (HPA) axis. Therapy should be discontinued when control of the disease is achieved. If no improvement is seen within 2 weeks, reassessment of the diagnosis may be necessary. Do not use more than half of the 120 g tube per week.

CONTRAINDICATIONS

VANOS Cream is contraindicated in those patients with a history of hypersensitivity to any of the components of the preparation.

PRECAUTIONS

General

Systemic absorption of topical corticosteroids can produce reversible hypothalamic-pituitary-adrenal (HPA) axis suppression with the potential for gluococorticosteroid insufficiency after withdrawal of treatment. Manifestations of Cushing's syndrome, hyperglycemia, and glucosuria can also be produced in some patients by systemic absorption of topical corticosteroids while on treatment. Use of more than one corticosteroid-containing product at the same time may increase total systemic glucocorticoid exposure. In addition, use of VANOS Cream for longer than 2 weeks may also suppress the immune system (see PRECAUTIONS: Carcinogenesis, Mutagenesis, and Impairment of Fertility).

Patients applying a topical steroid to a large surface area or to areas under occlusion should be evaluated periodically for evidence of HPA-axis suppression. This may be done by using cosyntropin (ACTH1–24) stimulation testing. Patients should not be treated with VANOS Cream for more than 2 weeks at a time and only small areas should be treated at any time due to the increased risk of HPA-axis suppression.

If HPA-axis suppression is noted, an attempt should be made to withdraw the drug, to reduce the frequency of application, or to substitute a less potent corticosteroid. Recovery of HPA-axis function is generally prompt upon discontinuation of topical corticosteroids. Infrequently, signs and symptoms of glucocorticosteroid insufficiency may occur requiring supplemental systemic corticosteroids. For information on systemic supplementation, see prescribing information for those products.

Application of VANOS Cream, 0.1% twice daily for 14 days in 18 adult patients with plaque-type psoriasis (10–50% BSA, mean 19.6% BSA) and 31 adult patients (17 treated once daily; 14 treated twice daily) with atopic dermatitis (2–10% BSA, mean 5% BSA) showed demonstrable HPA-axis suppression in 2 patients with psoriasis (with 12% and 25% BSA) and 1 patient with atopic dermatitis (treated once daily, 4% BSA) where the criterion for HPA-axis suppression is a serum cortisol level of less than or equal to 18 micrograms per deciliter 30 minutes after stimulation with cosyntropin (ACTH1–24) (See CLINICAL PHARMACOLOGY).

Controlled clinical efficacy studies of VANOS Cream in pediatric patients younger than 17 years of age have not been conducted; (See PRECAUTIONS: Pediatric Use).

HPA-axis suppression has not been evaluated in psoriasis patients who are less than 18 years of age.

Pediatric patients may be more susceptible to systemic toxicity from equivalent doses due to their larger skin surface to body mass ratios. (See PRECAUTIONS: Pediatric Use).

If irritation develops, VANOS Cream should be discontinued and appropriate therapy instituted. Allergic contact dermatitis with corticosteroids is usually diagnosed by observing failure to heal rather than noting a clinical exacerbation as with most topical products not containing corticosteroids. Such an observation should be corroborated with appropriate diagnostic patch testing.

If concomitant skin infections are present or develop, an appropriate antifungal or antibacterial agent should be used. If a favorable response does not occur promptly, use of VANOS Cream should be discontinued until the infection has been adequately controlled.

VANOS Cream should not be used in the treatment of rosacea or perioral dermatitis, and should not be used on the face, groin, or axillae.

Information for the Patient

Patients using VANOS Cream should receive the following information and instructions. This information is intended to aid in the safe and effective use of this medication. It is not a disclosure of all possible adverse or unintended effects:

1) VANOS Cream is to be used as directed by the physician. It is for external use only. Avoid contact with the eyes. It should not be used on the face, groin, and underarms.
2) VANOS Cream should not be used for any disorder other than that for which it was prescribed.
3) The treated skin area should not be bandaged or otherwise covered or wrapped, so as to be occlusive unless directed by the physician.
4) Patients should report to their physician any signs of local adverse reactions.
5) Other corticosteroid-containing products should not be used with VANOS Cream without first talking to the physician.
6) As with other corticosteroids, therapy should be discontinued when control is achieved. If no improvement is seen in 2 weeks, the patient should be instructed to contact a physician. The safety of the use of VANOS Cream for longer than 2 weeks has not been established.
7) Patients should be informed to not use more than 60 g per week of VANOS Cream. Do not use more than half of the 120 g tube per week.
8) Patients should inform their physicians that they are using VANOS Cream if surgery is contemplated.
9) Patients should wash their hands after applying medication.

Laboratory Tests

The cosyntropin (ACTH1–24) stimulation test may be helpful in evaluating patients for HPA-axis suppression.

Carcinogenesis, M utagenesis, and Impairment of Fertility

Long-term animal studies have not been performed to evaluate the carcinogenic potential of VANOS Cream because of severe immunosuppression induced in a 13-week dermal rat study. The effects of fluocinonide on fertility have not been evaluated.

Fluocinonide revealed no evidence of mutagenic or clastogenic potential based on the results of two in vitro genotoxicity tests (Ames test and chromosomal aberration assay using human lymphocytes). However, fluocinonide was positive for clastogenic potential when tested in the in vivo mouse micronucleus assay.

Topical (dermal) application of 0.0003%–0.03% fluocinonide cream to rats once daily for 13 weeks resulted in a toxicity profile generally associated with long-term exposure to corticosteroids including decreased skin thickness, adrenal atrophy, and severe immunosuppression. A NOAEL could not be determined in this study. In addition, topical (dermal) application of 0.1% fluocinonide cream plus UVR exposure to hairless mice for 13 weeks and 150–900 mg/kg/day of 0.1% fluocinonide cream to minipigs (a model which more closely approximates human skin) for 13 weeks produced glucocorticoid-related suppression of the HPA axis, with some signs of immunosuppression noted in the dermal minipig study. Although the clinical relevance of the findings in animals to humans is not clear, sustained glucocorticoid-related immune suppression may increase the risk of infection and possibly the risk for carcinogenesis.

Pregnancy Category C

Teratogenic Effects

Corticosteroids have been shown to be teratogenic in laboratory animals when administered systemically at relatively low dosage levels. Some corticosteroids have been shown to be teratogenic after dermal application in laboratory animals.

There are no adequate and well-controlled studies in pregnant women. Therefore, VANOS Cream should be used during pregnancy only if the potential benefit justifies the potential risk to the fetus.

Nursing Mothers

Systemically administered corticosteroids appear in human milk and could suppress growth, interfere with endogenous corticosteroid production, or cause other untoward effects. It is not known whether topical administration of corticosteroids could result in sufficient systemic absorption to produce detectable quantities in breast milk. Nevertheless, a decision should be made whether to discontinue nursing or to discontinue the drug, taking into account the importance of the drug to the mother.

Pediatric Use

Safety and efficacy of VANOS Cream in pediatric patients younger than 12 years of age have not been established; therefore use in pediatric patients younger than 12 years of age is not recommended.

HPA-axis suppression was studied in 4 sequential cohorts of pediatric patients with atopic dermatitis covering at least 20% of the body surface area, treated once daily or twice daily with VANOS Cream. The first cohort of 31 patients (mean 36.3% BSA) 12 to < 18 years old; the second cohort included 31 patients (mean 39.0% BSA) 6 to < 12 years old; the third cohort included 30 patients (mean 34.6% BSA) 2 to < 6 years old; the fourth cohort included 31 patients (mean 40.0% BSA) 3 months to < 2 years old. VANOS Cream caused HPA-axis suppression in 1 patient in the twice daily group in Cohort 1, 2 patients in the twice daily group in Cohort 2, and 1 patient in the twice daily group in Cohort 3. Follow-up testing 14 days after treatment discontinuation, available for all 4 suppressed patients, demonstrated a normally responsive HPA-axis. Signs of skin atrophy were present at baseline and severity was not determined making it difficult to assess local skin safety. Therefore, the safety of VANOS Cream in patients younger than 12 years of age has not been demonstrated.

Because of a higher ratio of skin surface area to body mass, pediatric patients are at a greater risk than adults of HPA-axis suppression and Cushing's syndrome when they are treated with topical corticosteroids. They are therefore also at greater risk of adrenal insufficiency during or after withdrawal of treatment. Adverse effects including striae have been reported with inappropriate use of topical corticosteroids in infants and children.

HPA-axis suppression, Cushing's syndrome, linear growth retardation, delayed weight gain, and intracranial hypertension have been reported in children receiving topical corticosteroids. Manifestations of adrenal suppression in children include low plasma cortisol levels and absence of response to cosyntropin (ACTH1–24) stimulation. Manifestations of intracranial hypertension include bulging fontanelles, headaches, and bilateral papilledema.

Geriatric Use

Clinical studies of VANOS Cream did not include sufficient numbers of subjects aged 65 and over to determine whether they respond differently from younger subjects. In general, dose selection for an elderly patient should be cautious.

ADVERSE REACTIONS

In clinical trials, a total of 443 adult patients with atopic dermatitis or plaque-type psoriasis were treated once daily or twice daily with VANOS Cream for 2 weeks. The most commonly observed adverse events in these clinical trials were as follows:

Table 3: Most Commonly Observed Adverse Events in Adult Clinical Trials
Adverse Event | VANOS Cream, once daily (n=216) | VANOS Cream, twice daily (n=227) | Vehicle Cream, once or twice daily (n=211)
Headache | 8/216 (3.7%) | 9/227 (4.0%) | 6/211 (2.8%)
Application Site Burning | 5/216 (2.3%) | 4/227 (1.8%) | 14/211 (6.6%)
Nasopharyngitis | 2/216 (0.9%) | 3/227 (1.3%) | 3/211 (1.4%)
Nasal Congestion | 3/216 (1.4%) | 1/227 (0.4%) | 0
Unspecified Application Site Reaction | 1/216 (0.4%) | 1/227 (0.4%) | 3/211 (1.4%)

No other adverse events were reported by more than 1 subject receiving active treatment. The incidence of all adverse events was similar between the active treatment groups and the vehicle control groups. Safety in patients 12 to 17 years of age was similar to that observed in adults.

The following additional local adverse reactions have been reported with topical corticosteroids, and they may occur more frequently with the use of occlusive dressings and higher potency corticosteroids. These reactions are listed in an approximate decreasing order of occurrence: burning, itching, irritation, dryness, folliculitis, hypertrichosis, acneiform eruptions, hypopigmentation, perioral dermatitis, allergic contact dermatitis, maceration of the skin, secondary infection, skin atrophy, striae, and miliaria.

Systemic absorption of topical corticosteroids has produced hypothalamic-pituitary-adrenal (HPA) axis suppression manifestations of Cushing's syndrome, hyperglycemia, and glucosuria in some patients.

OVERDOSAGE

Topically applied VANOS Cream can be absorbed in sufficient amounts to produce systemic effects (see PRECAUTIONS).

DOSAGE AND ADMINISTRATION

For psoriasis, apply a thin layer of VANOS Cream once or twice daily to the affected skin areas as directed by a physician. Twice daily application for the treatment of psoriasis has been shown to be more effective in achieving treatment success during 2 weeks of treatment.

For atopic dermatitis, apply a thin layer of VANOS Cream once daily to the affected skin areas as directed by a physician. Once daily application for the treatment of atopic dermatitis has been shown to be as effective as twice daily treatment in achieving treatment success during 2 weeks of treatment (See CLINICAL STUDIES).

For corticosteroid responsive dermatoses, other than psoriasis or atopic dermatitis, apply a thin layer of VANOS Cream once or twice daily to the affected areas as directed by a physician.

Treatment with VANOS Cream should be limited to 2 consecutive weeks, and no more than 60 g/week should be used. Do not use more than half of the 120 g tube per week.

Therapy should be discontinued when control has been achieved. If no improvement is seen within 2 weeks, reassessment of diagnosis may be necessary.

HOW SUPPLIED

VANOS (fluocinonide) Cream 0.1% is supplied in tubes as follows:

60 g (NDC 54868-6204-0)

STORAGE AND HANDLING

Store at controlled room temperature: 15° to 30°C (59° to 86°F).

Manufactured for:
Medicis, The Dermatology Company
Scottsdale, AZ 85256

Manufactured by:
Contract Pharmaceuticals Ltd.
Mississauga, Ontario
Canada L5N 6L6

Made in Canada

U.S. Patents 6,765,001; 7,217,422; 7,220,424 and Patents Pending
VANOS is a registered trademark of Medicis Pharmaceutical Corporation.

Prescribing information as of February 2010.

05100002

Relabeling of "Additional Barcode Label" by:
Physicians Total Care, Inc.
Tulsa, OK 74146

PRINCIPAL DISPLAY PANEL - 60 g Tube Carton

Vanos®
(fluocinonide) cream 0.1%

FOR TOPICAL USE ONLY
NOT FOR OPHTHALMIC, ORAL,
OR INTRAVAGINAL USE

Rx only

60 g